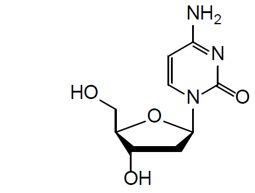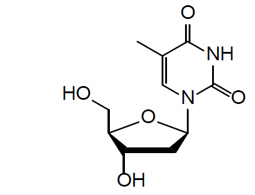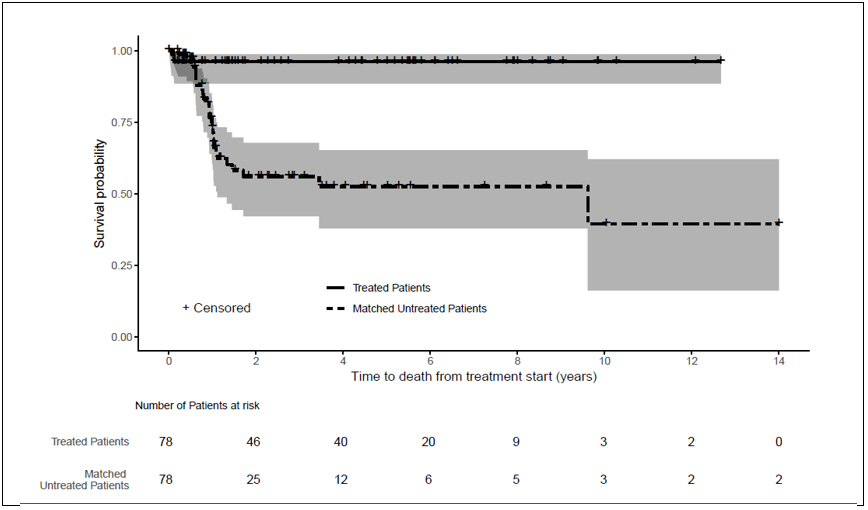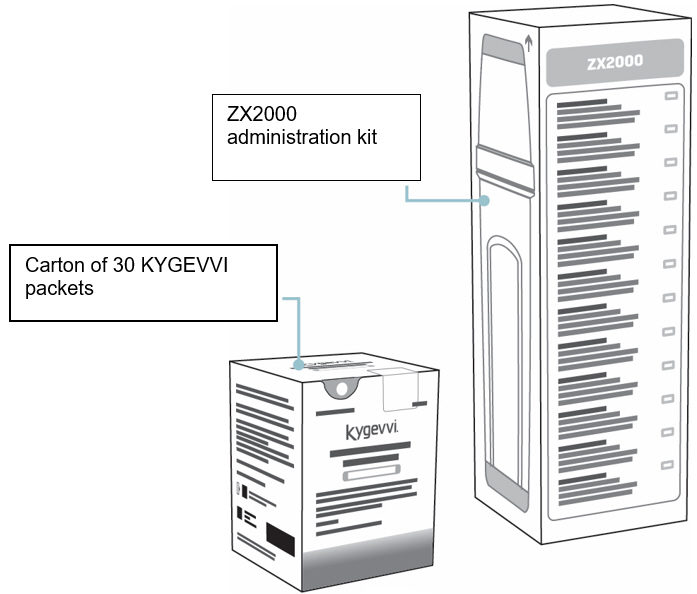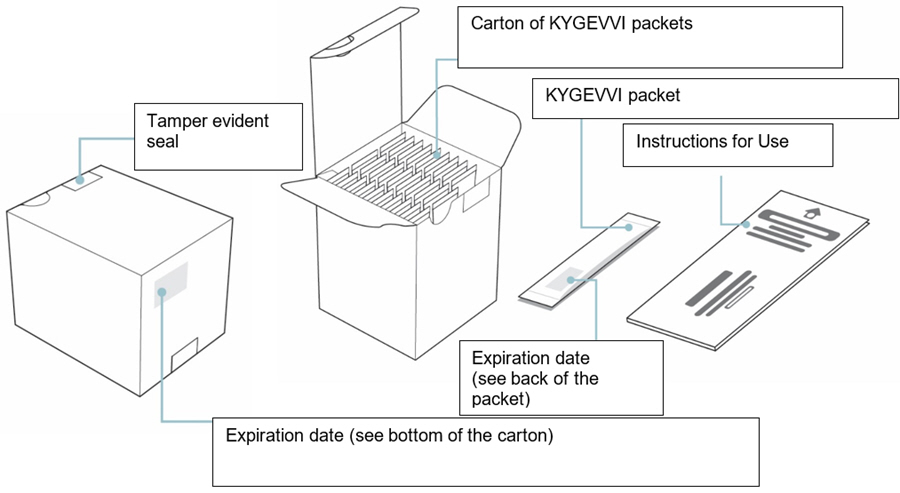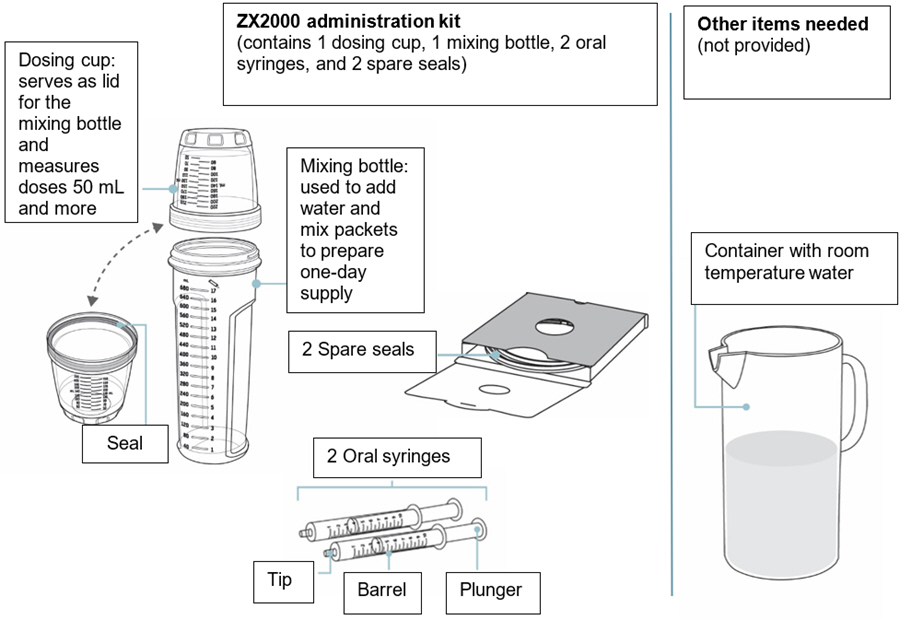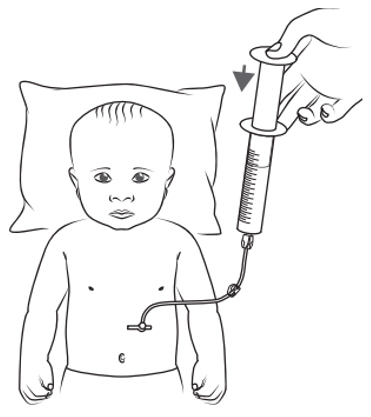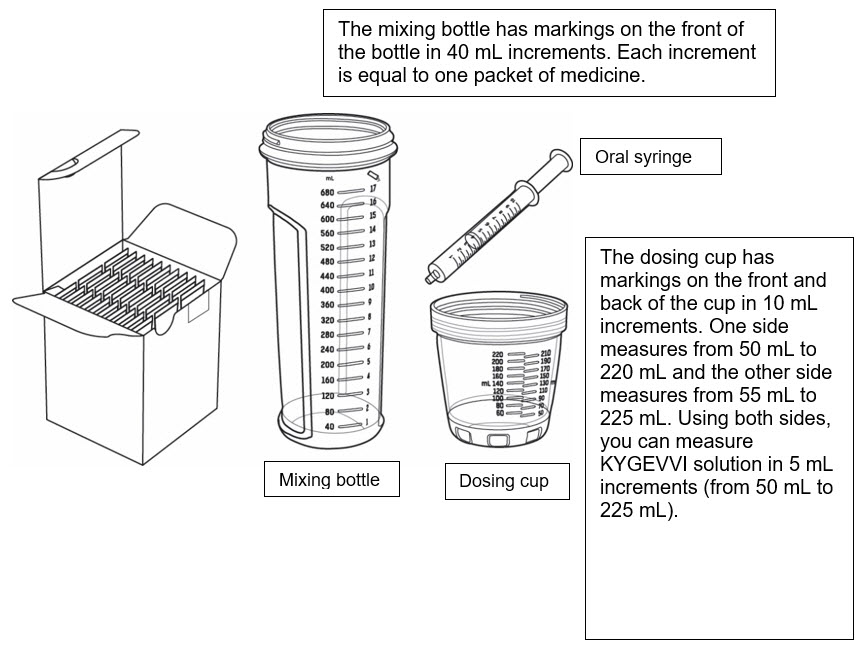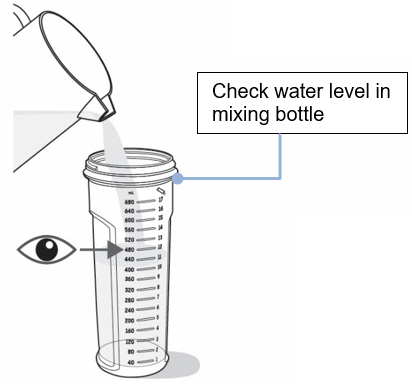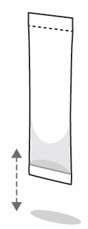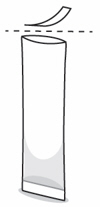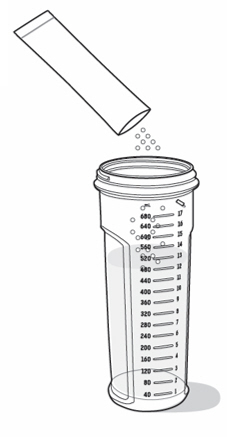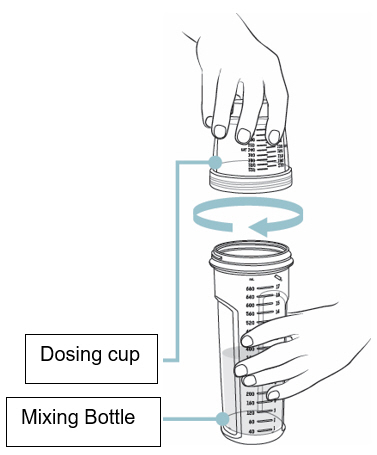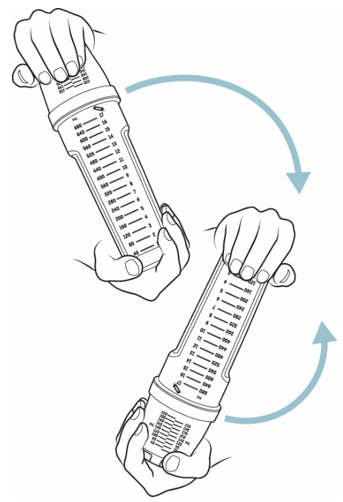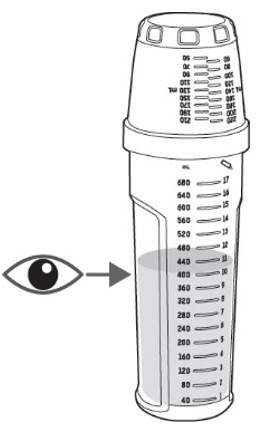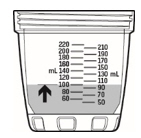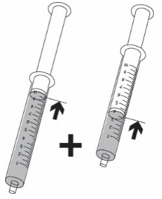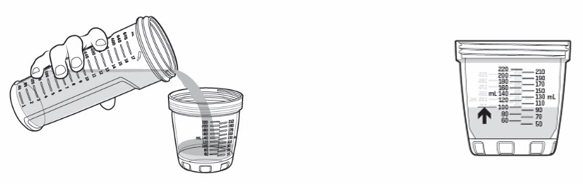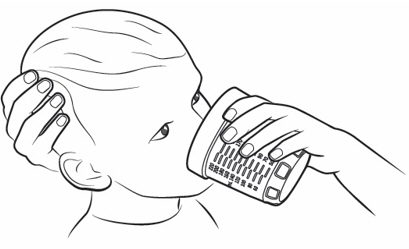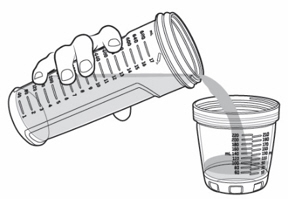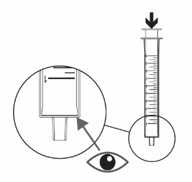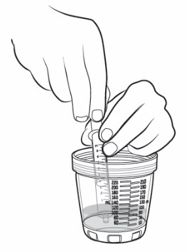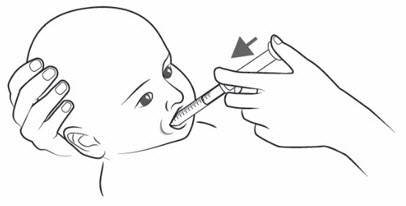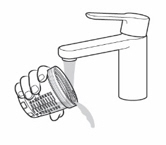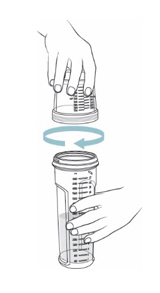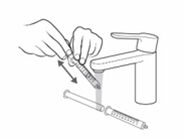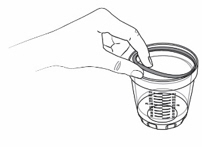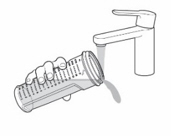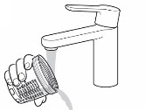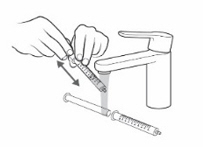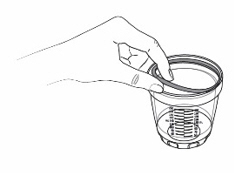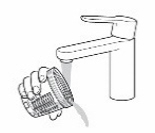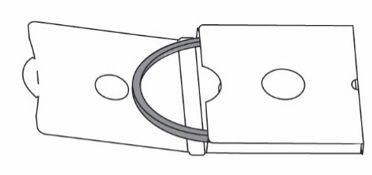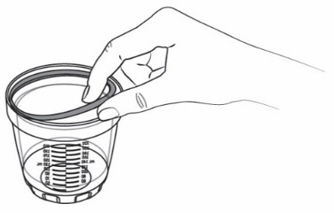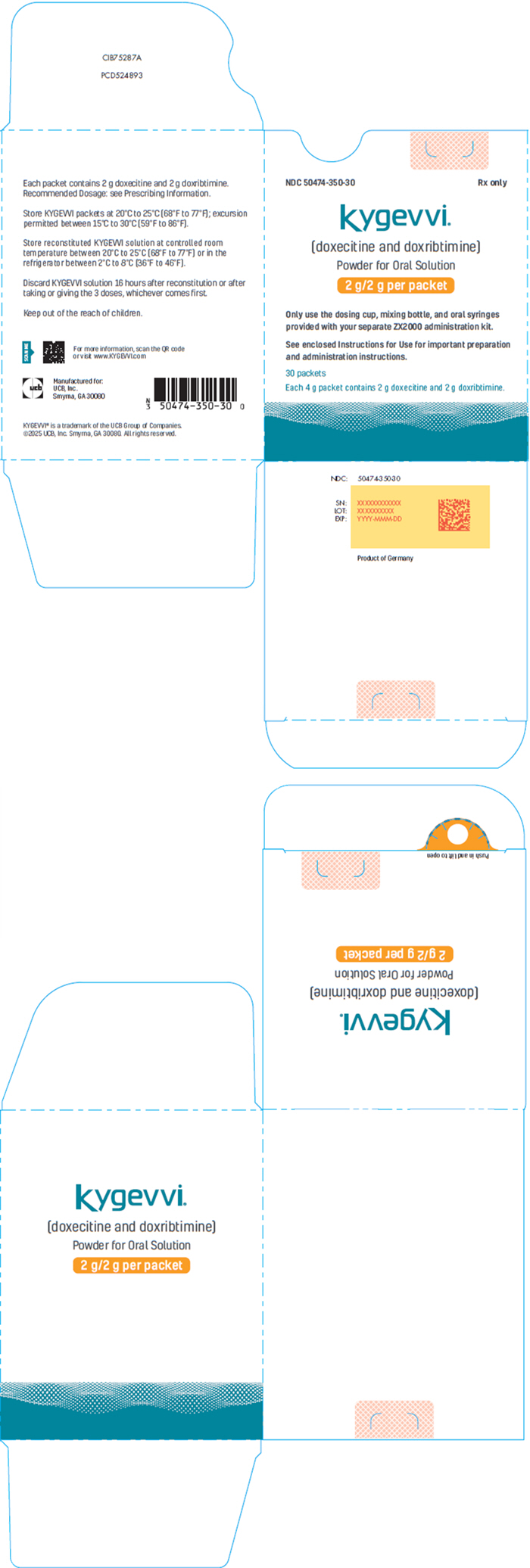 DRUG LABEL: KYGEVVI
NDC: 50474-350 | Form: POWDER, FOR SOLUTION
Manufacturer: UCB, Inc.
Category: prescription | Type: HUMAN PRESCRIPTION DRUG LABEL
Date: 20251110

ACTIVE INGREDIENTS: DOXECITINE 2 g/1 1; DOXRIBTIMINE 2 g/1 1

HIGHLIGHTS OF PRESCRIBING INFORMATION

These highlights do not include all the information needed to use KYGEVVI safely and effectively. See full prescribing information for KYGEVVI.
KYGEVVI (doxecitine and doxribtimine) powder, for oral solution
Initial U.S. Approval: 2025

1 INDICATIONS AND USAGE

KYGEVVI is a combination of doxecitine and doxribtimine, both pyrimidine nucleosides, indicated for the treatment of thymidine kinase 2 deficiency (TK2d) in adults and pediatric patients with an age of symptom onset on or before 12 years. (1)

2 DOSAGE AND ADMINISTRATION

- Obtain baseline transaminase (alanine aminotransferase [ALT] and aspartate aminotransferase [AST]) levels in all patients prior to treatment initiation. (2.1)
- Recommended dosage (2.2):
  KYGEVVI Dosage Level | KYGEVVI Dosage (mg/kg/day)
  Starting | 260 mg/kg/day (consisting of 130 mg doxecitine and 130 mg doxribtimine)
  Intermediate | 520 mg/kg/day (consisting of 260 mg doxecitine and 260 mg doxribtimine)
  Maintenance | 800 mg/kg/day (consisting of 400 mg doxecitine and 400 mg doxribtimine)
- Titrate to the next dosage level based on tolerability after a minimum of 2 weeks at the current dosage level. (2.2)
- Administer KYGEVVI orally in 3 equally divided doses with food. (2.2)
- See full prescribing information for dosage and administration modifications, monitoring, and preparation and administration instructions. (2.4)
- Use KYGEVVI only with ZX2000 administration kit. (2.4)

3 DOSAGE FORMS AND STRENGTHS

Powder for oral solution: 2 g doxecitine and 2 g doxribtimine. (3)

4 CONTRAINDICATIONS

- None. (4)

5 WARNINGS AND PRECAUTIONS

- Elevated Liver Transaminase Levels: Obtain baseline liver transaminase (ALT, AST) and total bilirubin levels prior to treatment initiation with KYGEVVI. If signs or symptoms consistent with liver injury are observed, interrupt treatment. Consider permanently discontinuing KYGEVVI if signs/symptoms consistent with liver injury persist or worsen. Monitor patients yearly and as clinically indicated. (5.1)
- Gastrointestinal Adverse Reactions: Reduce KYGEVVI dosage or interrupt treatment based on severity of diarrhea and/or vomiting. If persistent severe diarrhea and/or vomiting occurs, consider discontinuing KYGEVVI permanently. (5.2)

6 ADVERSE REACTIONS

Most common adverse reactions (incidence ≥5%) are diarrhea, abdominal pain (including abdominal pain upper), vomiting, alanine aminotransferase increased (ALT), and aspartate aminotransferase increased (AST). (6.1)

To report SUSPECTED ADVERSE REACTIONS, contact UCB, Inc. at 1-844-599-2273 or FDA at 1-800-FDA-1088 or www.fda.gov/medwatch.

FULL PRESCRIBING INFORMATION

1 INDICATIONS AND USAGE

KYGEVVI is indicated for the treatment of thymidine kinase 2 deficiency (TK2d) in adults and pediatric patients with an age of symptom onset on or before 12 years.

2 DOSAGE AND ADMINISTRATION

2.1 Important Recommendation Prior to KYGEVVI Treatment Initiation

Obtain baseline liver transaminase (alanine aminotransferase [ALT] and aspartate aminotransferase [AST]) and total bilirubin levels in patients prior to treatment initiation with KYGEVVI [see Dosage and Administration (2.3)and Warnings and Precautions (5.1)] .

2.2 Recommended Dosage

The recommended dosage of KYGEVVI is based on the patient's weight (Table 1). Titrate to the next dosage level based on tolerability after a minimum of 2 weeks at the current dosage level.

Table 1: Recommended Starting, Intermediate, and Maintenance Dosage of KYGEVVI
KYGEVVI Dosage Level | KYGEVVI Dosage (mg/kg/day)
Starting | 260 mg/kg/day (consisting of 130 mg doxecitine and 130 mg doxribtimine)
Intermediate | 520 mg/kg/day (consisting of 260 mg doxecitine and 260 mg doxribtimine)
Maintenance | 800 mg/kg/day (consisting of 400 mg doxecitine and 400 mg doxribtimine)

Administer KYGEVVI orally in 3 equally divided doses approximately 6 hours apart (plus or minus 2 hours) with food [see Clinical Pharmacology (12.3)] .

After calculating the daily dose, use Table 2 to determine the required number of KYGEVVI packets, volume of water needed to reconstitute the powder from the packet(s), and individual volume that is administered 3 times a day [see Dosage and Administration (2.4)].

2.3 Dosage and Administration Modifications and Monitoring

Liver Test Abnormalities

If signs or symptoms consistent with liver injury are observed, interrupt treatment with KYGEVVI until liver transaminase (ALT, AST) and total bilirubin levels have either returned to baseline or stabilized at a new baseline value. Consider re-starting KYGEVVI at the last tolerated dose and increase the dose based on tolerability [see Dosage and Administration (2.2)] . Consider permanently discontinuing KYGEVVI if signs or symptoms consistent with liver injury persist or worsen. Monitor liver transaminases and total bilirubin levels yearly and as clinically indicated [see Warnings and Precautions (5.1)] .

Gastrointestinal

Based on the severity of the diarrhea and/or vomiting, reduce the dose of KYGEVVI or interrupt treatment until diarrhea and/or vomiting improves or returns to baseline. Consider re-starting KYGEVVI at the last tolerated dose and increase the dose based on tolerability [see Dosage and Administration (2.2)] . For persistent or recurring diarrhea and/or vomiting, consider discontinuing KYGEVVI permanently. Monitor for dehydration and treat promptly with electrolyte replacement [see Warnings and Precautions (5.2)] .

2.4 Preparation and Administration Instructions

Use Table 2 for preparation and administration information.

Table 2: Recommended Dosage - Preparation and Dosing by Daily-Dose Range
Total Daily Dose (mg/day) | Volume of Solution (mL) (administered 3 times per day) | Total mL of Water for Reconstitution | Total Number of KYGEVVI Packets for Reconstitution
750 – 824 | 2.5 | 40 | 1
825 – 974 | 3 | 40 | 1
975 – 1,124 | 3.5 | 40 | 1
1,125 – 1,299 | 4 | 40 | 1
1,300 – 1,449 | 4.5 | 40 | 1
1,450 – 1,649 | 5 | 40 | 1
1,650 – 1,949 | 6 | 40 | 1
1,950 – 2,249 | 7 | 40 | 1
2,250 – 2,549 | 8 | 40 | 1
2,550 – 2,849 | 9 | 40 | 1
2,850 – 3,149 | 10 | 40 | 1
3,150 – 3,449 | 11 | 40 | 1
3,450 – 3,749 | 12 | 40 | 1
3,750 – 4,049 | 13 | 40 | 1
4,050 – 4,349 | 14 | 80 | 2
4,350 – 4,649 | 15 | 80 | 2
4,650 – 4,949 | 16 | 80 | 2
4,950 – 5,249 | 17 | 80 | 2
5,250 – 5,549 | 18 | 80 | 2
5,550 – 5,849 | 19 | 80 | 2
5,850 – 6,149 | 20 | 80 | 2
6,150 – 6,449 | 21 | 80 | 2
6,450 – 6,749 | 22 | 80 | 2
6,750 – 7,049 | 23 | 80 | 2
7,050 – 7,349 | 24 | 80 | 2
7,350 – 7,649 | 25 | 80 | 2
7,650 – 7,949 | 26 | 80 | 2
7,950 – 8,249 | 27 [The volume of each individual dose, when multiplied by 3, may not match the corresponding water volume used in the preparation of the oral solution as the final volume of the reconstituted oral solution will increase after the powder from the packets is added to the water volume.] | 80 | 2
8,250 – 8,549 | 28 | 120 | 3
8,550 – 8,849 | 29 | 120 | 3
8,850 – 9,749 | 30 | 120 | 3
9,750 – 11,249 | 35 | 120 | 3
11,250 – 12,749 | 40 | 120 | 3
12,750 – 14,249 | 45 | 160 | 4
14,250 – 15,749 | 50 | 160 | 4
15,750 – 17,249 | 55 | 160 | 4
17,250 – 18,749 | 60 | 200 | 5
18,750 – 20,249 | 65 | 200 | 5
20,250 – 21,749 | 70 | 200 | 5
21,750 – 23,249 | 75 | 240 | 6
23,250 – 24,749 | 80 | 240 | 6
24,750 – 26,249 | 85 | 280 | 7
26,250 – 27,749 | 90 | 280 | 7
27,750 – 29,249 | 95 | 280 | 7
29,250 – 30,749 | 100 | 320 | 8
30,750 – 32,249 | 105 | 320 | 8
32,250 – 33,749 | 110 | 320 | 8
33,750 – 35,249 | 115 | 360 | 9
35,250 – 36,749 | 120 | 360 | 9
36,750 – 38,249 | 125 | 360 | 9
38,250 – 39,749 | 130 | 400 | 10
39,750 – 41,249 | 135 | 400 | 10
41,250 – 42,749 | 140 | 400 | 10
42,750 – 44,249 | 145 | 440 | 11
44,250 – 45,749 | 150 | 440 | 11
45,750 – 47,249 | 155 | 440 | 11
47,250 – 48,749 | 160 | 480 | 12
48,750 – 50,249 | 165 | 480 | 12
50,250 – 51,749 | 170 | 480 | 12
51,750 – 53,249 | 175 | 520 | 13
53,250 – 54,749 | 180 | 520 | 13
54,750 – 56,249 | 185 | 560 | 14
56,250 – 57,749 | 190 | 560 | 14
57,750 – 59,249 | 195 | 560 | 14
59,250 – 60,749 | 200 | 600 | 15
60,750 – 62,249 | 205 | 600 | 15
62,250 – 63,749 | 210 | 600 | 15
63,750 – 65,249 | 215 | 640 | 16
65,250 – 66,749 | 220 | 640 | 16
66,750 – 68,249 | 225 | 640 | 16

Use the ZX2000 administration kit provided separately to prepare and administer the prescribed dose [see How Supplied/Storage and Handling (16)] . Refer to the Instructions for Use for full preparation and administration information on use of KYGEVVI with the ZX2000 administration kit. Household devices such as measuring cups or spoons are not adequate measuring devices. KYGEVVI should be prepared and administered by adults only.

Preparation Instructions

Preparation of KYGEVVI with a liquid other than water has not been studied clinically and is not recommended.

1. Obtain the required number of KYGEVVI packets to prepare a one-day supply of solution each morning.
2. Use 40 mL of water per packet. Pour the prescribed volume of room temperature water (between 20°C - 25°C or 68°F - 77°F) into the mixing bottle.
3. Add the powder from the required number of KYGEVVI packets into the mixing bottle.
4. Screw the dosing cup tightly onto the mixing bottle and gently invert the mixing bottle back and forth at least 20 times. If powder remains, repeat until the powder dissolves.
5. The mixed solution may appear cloudy and have some residual powder (inactive ingredients) remaining at the bottom or top.

Administration Instructions

Oral Administration

1. Before each administration, gently invert the tightly closed mixing bottle slowly back and forth at least 3 times.
2. Use 1 of 2 methods (dosing cup or oral syringe) to administer KYGEVVI solution. Choose the method based on the volume of solution to be administered per dose.
3. Take KYGEVVI solution in 3 equally divided doses approximately 6 hours apart (plus or minus 2 hours) with food.
4. Do not administer another dose if the dose is spit out or if a complete dose is not taken. Take the next dose at the next scheduled time.
5. Discard any remaining KYGEVVI solution 16 hours after reconstitution or after taking or giving the 3 doses, whichever comes first.

Feeding Tube Administration

KYGEVVI is compatible with most commonly available feeding tubes. KYGEVVI is compatible with feeding tubes made with polyvinylchloride (PVC) free from DEHP (Phthalates), polyurethane (PUR), and silicone (SIL) material.

1. Follow the instructions of the feeding tube manufacturer to administer KYGEVVI.
2. Draw up the KYGEVVI solution using a syringe compatible with the feeding tube.
3. Administer the solution immediately through the feeding tube.
4. Flush any residual solution in the syringe or feeding tube until no solution is left. To flush the tube, a single flushing step with a volume of water equivalent to the tube's priming volume is sufficient.
5. Discard any remaining KYGEVVI solution 16 hours after reconstitution or after taking or giving the 3 doses, whichever comes first.

2.5 Storage Instructions for Prepared KYGEVVI Solution

- Store reconstituted KYGEVVI solution at controlled room temperature between 20°C to 25°C (68°F to 77°F) or in the refrigerator between 2°C to 8°C (36°F to 46°F).
- Discard KYGEVVI solution 16 hours after reconstitution or after taking or giving the 3 doses, whichever comes first.

2.6 Missed Dose

If a dose is missed, take the missed dose as soon as possible but do not take within 2 hours of the next scheduled dose. In that case, skip the missed dose and resume the regular schedule. A double dose should not be taken to make up for the missed dose.

3 DOSAGE FORMS AND STRENGTHS

Powder for oral solution: 2 g doxecitine and 2 g doxribtimine as white to off-white powder in a single use packet.

4 CONTRAINDICATIONS

None.

5 WARNINGS AND PRECAUTIONS

5.1 Elevated Liver Transaminase Levels

Elevated liver transaminase [alanine aminotransferase (ALT) and/or aspartate aminotransferase (AST)] levels were reported in patients treated with KYGEVVI [see Adverse Reactions (6.1)] . In Study 1, two patients permanently discontinued treatment with KYGEVVI upon recurrence of elevated liver enzymes after a rechallenge at a reduced dose.

Obtain baseline liver transaminase (ALT, AST) and total bilirubin levels in patients prior to treatment initiation with KYGEVVI. If signs or symptoms consistent with liver injury are observed, interrupt treatment with KYGEVVI until liver transaminase (ALT, AST) and total bilirubin levels have either returned to baseline or stabilized at a new baseline value. Consider permanently discontinuing KYGEVVI if signs or symptoms consistent with liver injury persist or worsen. Monitor liver transaminases and total bilirubin levels yearly and as clinically indicated [see Dosage and Administration (2.3)] .

5.2 Gastrointestinal Adverse Reactions

Diarrhea and vomiting leading to hospitalization, dose reduction, and permanent discontinuation were reported in patients treated with KYGEVVI [see Adverse Reactions (6.1)] .

Based on the severity of the diarrhea and/or vomiting, reduce the dosage of KYGEVVI or interrupt treatment until diarrhea and/or vomiting improves or returns to baseline. Consider restarting KYGEVVI at the last tolerated dose, and increase the dose as tolerated. For persistent or recurring diarrhea and/or vomiting, consider discontinuing KYGEVVI permanently and provide supportive care with electrolyte repletion as clinically indicated.

6 ADVERSE REACTIONS

The following clinically significant adverse reactions are described elsewhere in the labeling:

- Elevated Liver Transaminase Levels [see Warnings and Precautions (5.1)]
- Gastrointestinal Adverse Reactions [see Warnings and Precautions (5.2)]

6.1 Clinical Trials Experience

Because clinical trials are conducted under widely varying conditions, adverse reaction rates observed in the clinical trials of a drug cannot be directly compared to rates in the clinical trials of another drug and may not reflect the rates observed in practice.

The safety of KYGEVVI was evaluated in a prospective, open-label, single-arm study in pediatric and adult patients with genetically confirmed TK2d previously treated with pyrimidine nucleosides (Trial 1). Additional safety information was derived from retrospective chart review studies (Study 1, Study 2) and from an expanded access program [see Clinical Studies (14)] .

Permanent discontinuation of KYGEVVI due to an adverse reaction occurred in 9% of patients (Trial 1, Study 1, and Study 2). The adverse reactions which resulted in permanent discontinuation of KYGEVVI in >2% of patients were diarrhea (3%) and elevated liver enzymes (3%). In the expanded access program, diarrhea resulted in permanent discontinuation in 2 patients.

Dose reductions of KYGEVVI due to an adverse reaction occurred in 22% of patients (Trial 1, Study 1, and Study 2). Adverse reactions which required dose reduction in >2% of patients included diarrhea (21%) and abdominal pain (3%).

Diarrhea resulted in hospitalization in 2 pediatric patients (Study 1 and expanded access program).

Adverse Reactions from Trial 1

A total of 47 patients, between the ages of 0.7 and 74 years of age at enrollment, received KYGEVVI or pyrimidine nucleosides dosages up to 800 mg/kg/day [see Clinical Studies (14)] . KYGEVVI is not approved for use in patients with an age of TK2d symptom onset > 12 years. The mean (SD) KYGEVVI or pyrimidine nucleosides exposure during Trial 1 was 6.6 (2) years.

Table 3 summarizes the adverse reactions reported in ≥ 5% patients treated with KYGEVVI or pyrimidine nucleosides.

Table 3: Adverse Reactions That Occurred in ≥5% Adult and Pediatric Patients with TK2d Treated with KYGEVVI or Pyrimidine Nucleosides (Trial 1)
Adverse reactions | Treated Patients (N=47) n (%)
Diarrhea | 34 (72)
Abdominal pain (including abdominal pain upper) | 11 (23)
Vomiting | 10 (21)
Alanine aminotransferase increased (ALT) | 10 (21)
Aspartate aminotransferase increased (AST) | 8 (17)

Adverse reactions, vomiting and elevated liver transaminases, were observed in a higher percentage of pediatric patients than in adult patients. In Trial 1, vomiting occurred in 28% (9/32) of pediatric patients compared to 7% (1/15) of adult patients. Elevated liver transaminases occurred in 25% (8/32) for ALT and 22% (7/32) for AST of pediatric patients compared to 13% (2/15) for ALT and 7% (1/15) for AST of adult patients.

Laboratory Adverse Reaction

Elevated liver enzymes have been observed as a clinical manifestation of TK2d. In Trial 1 and Study 1, elevations in alanine aminotransferase (ALT) and/or aspartate aminotransferase (AST) occurred in 28% (14/50) and 22% (11/50) of patients respectively. In Trial 1, of all the patients who started treatment with elevated AST/ALT at baseline, 5% had last post-baseline ALT values that were higher severity than the baseline severity while continuing treatment [see Warnings and Precautions (5.1)] .

8 USE IN SPECIFIC POPULATIONS

8.1 Pregnancy

Risk Summary

There are no available data on KYGEVVI use during pregnancy to evaluate for a drug-associated risk of major birth defects, miscarriage, or other adverse maternal or fetal outcomes. Endogenous pyrimidine nucleosides are transported across the placenta. There are risks for adverse maternal and fetal outcomes during pregnancy with mitochondrial myopathies, including TK2 deficiency (see Clinical Considerations). In animal reproduction studies, oral administration of doxecitine and doxribtimine to pregnant rats and rabbits during organogenesis resulted in maternal and fetal toxicities in the rabbit at dose exposures 1233 and 811 times the maximum recommended human dose (MRHD) of 400 mg/kg/day doxecitine and 400 mg/kg/day doxribtimine, respectively, based on plasma exposure, but were not observed in the rat (see Data).

The background risk of major birth defects and miscarriage for the indicated population is unknown. All pregnancies have a background risk of birth defect, loss, or other adverse outcomes. In the U.S. general population, the estimated background risk of major birth defects and miscarriage in clinically recognized pregnancies is 2% to 4% and 15% to 20% respectively.

Clinical Considerations

Disease-Associated Maternal and/or Embryo/Fetal Risk

Mitochondrial myopathies are associated with increased adverse perinatal outcomes, including preterm birth, pre-eclampsia and gestational diabetes.

Data

Animal Data

In an embryofetal development study in pregnant rats, once daily oral doses of 200, 600, and 2000 mg/kg/day doxecitine and doxribtimine were administered throughout organogenesis between gestation day (GD) 7 to 17. No maternal or embryofetal toxicity was observed up to 2000 mg/kg/day (1223 times and 425 times the MRHD of doxecitine and doxribtimine, respectively, based on plasma exposure).

In an embryofetal development study in pregnant rabbits, once daily oral doses of 200, 600, and 2000 mg/kg/day doxecitine and doxribtimine were administered throughout organogenesis between GD 7 and GD 19. Marked maternal toxicity and fetal malformations (dilated aorta with an associated narrow pulmonary trunk) were observed at the highest dose (1233 times and 811 times the MRHD of doxecitine and doxribtimine, respectively, based on plasma exposure). The maternal and fetal no observed adverse effect level (NOAEL) in rabbits (600 mg/kg/day) was associated with maternal plasma exposures 729 times and 126 times the MRHD of 400 mg/kg/day doxecitine and 400 mg/kg/day doxribtimine, respectively.

8.2 Lactation

Risk Summary

There are no data on the presence of doxecitine and doxribtimine or its metabolites in either human or animal milk, the effects on the breastfed infant, or the effects on milk production. Data from published literature reports the presence of nucleosides and nucleotides in human milk.

The developmental and health benefits of breastfeeding should be considered along with the mother's clinical need for KYGEVVI and any potential adverse effects on the breastfed infant from KYGEVVI or from the underlying maternal condition.

8.4 Pediatric Use

The safety and effectiveness of KYGEVVI for the treatment of thymidine kinase 2 deficiency (TK2d) have been established in pediatric patients with an age of symptom onset on or before 12 years. Use of KYGEVVI for this indication in this population is supported by evidence from two retrospective studies (Study 1, Study 2), one open-label study (Trial 1), and an expanded access program in which a total of 68 patients 0.7 years of age to less than 17 years of age were treated [see Clinical Studies (14)] .

In Trial 1, compared to adults, a higher percentage of pediatric patients experienced adverse reactions of vomiting and elevated liver transaminases [see Adverse Reactions (6.1)] . Serious adverse reactions in the pediatric population included hospitalization due to diarrhea in two patients [see Warnings and Precautions (5.2)] .

8.5 Geriatric Use

Clinical studies of KYGEVVI did not include sufficient number of patients 65 years of age and older to determine whether they respond differently from younger adult patients.

8.6 Renal Impairment

Plasma concentrations of doxecitine and doxribtimine increased in patients with moderate or severe renal impairment. The pharmacokinetics (PK) of doxecitine and doxribtimine have not been evaluated in patients with mild renal impairment. An appropriate dosage adjustment of KYGEVVI in patients with renal impairment could not be determined because renal impairment had distinct effects on the PK of doxecitine and PK of doxribtimine, and it is not feasible to separately adjust the dosage for doxecitine or doxribtimine contained in KYGEVVI [see Clinical Pharmacology (12.3)] .

11 DESCRIPTION

KYGEVVI is a combination of doxecitine and doxribtimine, both of which are pyrimidine nucleosides. KYGEVVI is a powder for oral solution. Both doxecitine and doxribtimine are white to off-white powders and soluble in water.

Doxecitine

The chemical name of doxecitine is 4-Amino-1-((2R,4S,5R)-4-hydroxy-5-(hydroxymethyl)tetrahydrofuran-2-yl)pyrimidin-2(1H)-one. The molecular formula is C9H13N3O4and the molecular weight is 227.22 g/mol. The chemical structure is:

Doxribtimine

The chemical name of doxribtimine is 1-((2R,4S,5R)-4-Hydroxy-5-(hydroxymethyl)tetrahydrofuran-2-yl)-5-methylpyrimidine-2,4(1H,3H)-dione. The molecular formula is C10H14N2O5and the molecular weight is 242.23 g/mol. The chemical structure is:

Each packet of KYGEVVI powder contains 2 grams doxecitine and 2 grams doxribtimine. The inactive ingredients are colloidal silicon dioxide and magnesium stearate.

12 CLINICAL PHARMACOLOGY

12.1 Mechanism of Action

Administration of KYGEVVI is intended to incorporate the pyrimidine nucleosides, deoxycytidine and deoxythymidine, into skeletal muscle mitochondrial deoxyribonucleic acid (DNA). This action restores mitochondrial DNA copy number in TK2d mutant mice.

12.2 Pharmacodynamics

The exposure-response relationship and time course of pharmacodynamic response for the safety and effectiveness of KYGEVVI have not been fully characterized.

12.3 Pharmacokinetics

Following oral administration of doxecitine and doxribtimine in healthy adult subjects, the baseline-adjusted maximum plasma concentration (Cmax) and area under the plasma concentration-time curve (AUC) increased in a less than dose proportional manner for doxecitine at doses ranging from 43 mg/kg to 133 mg/kg and more than dose proportional manner for doxribtimine at doses ranging from 43 mg/kg to 133 mg/kg. There is minimal or no accumulation of doxecitine and doxribtimine following multiple dose administrations. Following oral administration of doxecitine and doxribtimine at the recommended maintenance dosage of 800 mg/kg/day under fed conditions in 18 TK2d pediatric and adult subjects, the estimated baseline-unadjusted geometric mean Cmaxat steady state was 12 ng/mL and 19 ng/mL for doxecitine and doxribtimine, respectively, and the geometric mean AUC from time 0 to 24 hours (AUC0-24hr) was 108 ng∙h/mL and 191 ng∙h/mL for doxecitine and doxribtimine, respectively. Inter-subject variability (geometric CV%) in Cmaxand AUC0-24hvalues of doxecitine and doxribtimine were greater than 70%.

Absorption

The absolute bioavailability of doxecitine and doxribtimine following oral administration has not been determined. The median time to peak plasma concentration (Tmax) was approximately 2 hours for doxecitine and 4 hours for doxribtimine.

Effect of Food

Following an oral administration of 133 mg/kg doxecitine and 133 mg/kg doxribtimine with a high-fat, high-calorie meal in healthy adult subjects, baseline-adjusted plasma Cmaxand AUC0-tincreased by 79% and 137%, respectively, for doxecitine; and increased by 27% and 74%, respectively, for doxribtimine, compared to fasted conditions [see Dosage and Administration (2.2)] .

Distribution

In vitro plasma protein binding of doxecitine and doxribtimine was less than 10% over the concentration range between 0.23 mcg/mL and 23 mcg/mL.

Elimination

The mean half-life was approximately 1 hour for doxecitine and 5 hours for doxribtimine following a single oral administration of 133 mg/kg doxecitine and 133 mg/kg doxribtimine under fed conditions in healthy adult subjects.

Metabolism

Doxecitine and doxribtimine are primarily degraded (catabolized) by cytidine deaminase and thymidine phosphorylase, respectively, to their nucleobases and the 2-deoxy-α-D-ribose 1-phosphate moiety. Intermediate products of doxecitine catabolism are deoxyuridine, uracil, and dihydrouracil with the end products β-alanine, ammonia, and carbon dioxide (CO2). Thymine, the pyrimidine nucleobase of doxribtimine, is subsequently catabolized to dihydrothymine and ultimately to γ-amino-isobutyric acid and CO2.

Doxecitine and doxribtimine are not known to be metabolized by cytochrome P450 (CYP) isoforms.

Excretion

Urinary excretion of intact doxecitine and doxribtimine was <1% of the dose in healthy subjects following an oral administration of doxecitine and doxribtimine.

Specific Populations

Male and Female Patients

The pharmacokinetics of doxecitine and doxribtimine were not significantly different between male and female subjects.

Patients with Renal Impairment

The pharmacokinetics of doxecitine and doxribtimine in subjects with moderate (estimated glomerular filtration rate [eGFR] ≥ 30 and ≤ 59 mL/min/1.73 m^2) or severe (eGFR ≥ 15 and ≤ 29 mL/min/1.73 m^2) renal impairment were compared with healthy subjects with normal renal function following a single oral administration of 133 mg/kg doxecitine and 133 mg/kg doxribtimine. Baseline-adjusted plasma doxecitine AUC was 122% and 66% higher in subjects with moderate and severe renal impairment, respectively, compared with matched control subjects with normal renal function. Baseline adjusted plasma doxribtimine AUC was 447% and 148% higher in subjects with moderate and severe renal impairment, respectively, compared with matched control subjects with normal renal function [see Use in Specific Populations (8.6)] .

Patients with Hepatic Impairment

No studies have been conducted to evaluate the effect of hepatic impairment on the pharmacokinetics of doxecitine and doxribtimine.

Drug Interaction Studies

In Vitro Studies

CYP enzymes: Doxecitine and doxribtimine are not inducers, inhibitors, or substrates of CYP isozymes at clinically relevant concentrations.

Transporter systems: Doxecitine and doxribtimine do not inhibit P-glycoprotein (P-gp), BCRP, BSEP, OATP1B1, OATP1B3, OAT1, OAT3, OCT1, OCT2, MATE1, or MATE2-K at clinically relevant concentrations. Doxribtimine may be a substrate of BCRP, but its clinical significance is unknown.

13 NONCLINICAL TOXICOLOGY

13.1 Carcinogenesis, Mutagenesis, Impairment of Fertility

Carcinogenesis

Animal studies to evaluate the carcinogenic potential of doxecitine and doxribtimine have not been conducted.

Mutagenesis

Doxecitine and doxribtimine were not mutagenic or clastogenic in an in vitrobacterial reverse mutation (Ames) and an in vivorat micronucleus assay. Doxecitine and doxribtimine induced chromosomal aberrations in the absence of metabolic activation in an in vitrocytogenetic study in human lymphocytes. One compound (alpha-hydroxythymidine) originating from a doxribtimine starting material and present in the final drug product was positive for mutagenesis in the Ames assay and positive for clastogenesis in human peripheral lymphocytes when tested alone.

Impairment of Fertility

Doxecitine and doxribtimine had no effect on male or female fertility or early embryonic development at doses up to 2000 mg/kg/day in rats (1131 times and 1223 times the MRHD in males and females respectively for 400 mg/kg/day doxecitine and 1056 times and 425 times the MRHD in males and females respectively for 400 mg/kg/day doxribtimine, based on plasma exposure).

14 CLINICAL STUDIES

The efficacy of KYGEVVI for the treatment of patients with TK2d, with an age of symptom onset on or before 12 years of age, was established based on data from one Phase 2 clinical study (Trial 1), two retrospective chart review studies (Study 1, Study 2), and an expanded access program. The survival in treated patients was compared with survival in an untreated external control group comprised of untreated patients from published literature and Study 2.

Trial 1 (NCT03845712) is a prospective, open-label, single-arm study in 47 patients with genetically confirmed TK2d previously treated with pyrimidine nucleosides. Thirty-eight of these 47 patients have an age of TK2d symptom onset ≤12 years; none of the 38 patients discontinued treatment. The initial oral dose of KYGEVVI was matched to the patient's pyrimidine nucleoside dose of 260-800 mg/kg/day upon entering the study in patients with an age of TK2d symptom onset ≤ 12 years, and dosage was titrated, as needed, over a maximum of 4 weeks to the maintenance dose of 800 mg/kg/day.

Study 1 (NCT03701568) was a retrospective chart review study in 38 patients with genetically confirmed TK2d treated with pyrimidine nucleosides. Twenty-nine of these patients had an age of TK2d symptom onset ≤12 years; none of the 29 patients discontinued treatment. Thirty-five of these 38 patients were later enrolled in Trial 1 to receive treatment with KYGEVVI and one was later enrolled in Study 2. KYGEVVI was not administered in Study 1. Patients enrolled in Study 1 were receiving pyrimidine nucleoside treatment at doses 160-800 mg/kg/day.

Study 2 (NCT05017818) was a retrospective chart review study in 61 patients with genetically confirmed TK2d (43 untreated patients and 18 patients treated with pyrimidine nucleoside therapy). Nine of these 61 patients were also included in the expanded access program and 1 patient was included in Study 1. Twenty-seven of the 43 untreated patients had an age of TK2d symptom onset ≤12 years, and 13 of the 18 treated patients had an age of TK2d symptom onset ≤12 years. Twenty-two untreated patients were included in the untreated external control group used to evaluate survival. Of the 18 treated patients, 6 (33%) discontinued treatment due to an adverse reaction. KYGEVVI was not administered in Study 2. Patients enrolled in Study 2 were receiving pyrimidine nucleoside treatment at doses 200-1200 mg/kg/day.

Expanded Access Program

The expanded access program data included 43 patients receiving KYGEVVI; 9 patients were included in Study 2.

Efficacy Results

A total of 82 patients with genetically confirmed TK2d and the age of symptom onset ≤12 years were treated with KYGEVVI or pyrimidine nucleosides. Efficacy was assessed by comparing overall survival in the treated patients to an external control group of untreated patients matched to treated patients using age of TK2d symptom onset (≤ 2 years or >2 to ≤ 12 years). A total of 78 matched pairs were identified.

Of the 78 treated patients included in the survival analysis, 54% were male and 36% were of Hispanic or Latino ethnicity. Eighty-two percent of patients were White, 4% Black or African American, 5% Asian, 3% Other, and 1% American Indian or Alaska Native. The median age of TK2d symptom onset was 1.5 years (range: 0.01 to 12 years). The median duration of treatment was 4 years (range: 1 day to 12 years) and the median dose received was 762 mg/kg/day (range: 260 to 800 mg/kg/day).

Treatment reduced the overall risk of death from treatment start by approximately 86% (95% CI: 61%, 96%) (Table 4, Figure 1).

Table 4: Overall Survival in Patients with TK2d (Age of Symptom Onset ≤12 Years) Treated with KYGEVVI Versus Matched Untreated Patients (External Control) [Treated patients were originally from Trial 1 (n=9), Study 1 (n=27), Study 2 (n=11), and the expanded access program (n=31). Untreated patients were from published literature (n=57) and Study 2 (n=21).]
 | Treated Patients (n= 78) | Matched Untreated Patients (n=78)
Number of Deaths (%) [An additional censoring step for untreated subjects was performed for each matched pair where the untreated subject died and had a longer follow-up time than the matched treated subject who was censored. The follow-up time of the untreated subject was then censored at the follow-up time of the treated subject.] | 3 (3.8%) | 28 (35.9%)
Restricted Mean Survival Time in Years (95% CI) , [Based on the area under the survival curves up to 4-, 6-, 10-years post treatment start.]
- At 4 years post treatment start - At 6 years post treatment start - At 10 years post treatment start | - 3.8 (3.7, 4) - 5.8 (5.5, 6) - 9.6 (9.2, 10) | - 2.6 (2.2, 3) - 3.7 (3, 4.3) - 5.7 (4.5, 6.9)
Hazard Ratio [Estimates based on Cox Proportional Hazard Model with Firth correction that includes matched pair as a strata, age of symptom onset as a continuous covariate, and treatment (treated or untreated) as a time independent variable.]
For Risk of death from treatment start | 0.14 (0.04, 0.39)
(95%CI)
CI: Confidence Interval

Note: Treated patients were matched 1:1 to untreated patients by category of age of TK2d symptom onset (≤2 years or >2 to ≤12 years). Within each category of age of symptom onset, the matching was performed as follows: treated patients were sorted in descending order, according to their age of treatment initiation; the first treated patient in the sorted list was matched with the sorted untreated patient having the highest last known age; this matched untreated patient was then no longer available for matching with any remaining treated patients; the procedure continues in order through the sorted list of treated patients. Time of treatment start in the untreated patient was set to that of the matched treated patient.

Figure 1: Kaplan-Meier Survival Curves for Time to Death from Treatment Start in Patients with TK2d Treated with KYGEVVI and Matched Untreated Patients (External control) [Treated patients were from Trial 1, Study 1, Study 2, and the expanded access program. Untreated patients were from published literature and Study 2.] , [Kaplan-Meier Curves with 95% confidence intervals using log-log transformation and with treatment group as strata variable; Age of TK2d Symptom Onset ≤ 12 years. An additional censoring step for untreated subjects in the footnote (b) of Table 4 was performed.]

16 HOW SUPPLIED/STORAGE AND HANDLING

How Supplied

KYGEVVI is supplied as follows:

Package 1 of 2

NDC 50474-350-01: Each single use packet contains 4 g of KYGEVVI as a white to off-white powder (2 g doxecitine and 2 g doxribtimine)

NDC 50474-350-30: Carton contains 30 packets

Package 2 of 2

The ZX2000 administration kit for use with KYGEVVI is supplied separately and contains the following:

- One dosing system (includes mixing bottle and dosing cup)
- Two 10 mL oral syringes
- Two spare seals

Storage and Handling

Store KYGEVVI packets at 20°C to 25°C (68°F to 77°F); excursion permitted between 15°C to 30°C (59°F to 86°F) [see USP Controlled Room Temperature].

Store reconstituted KYGEVVI solution at controlled room temperature or in the refrigerator. Discard KYGEVVI solution 16 hours after reconstitution or after taking or giving the 3 doses, whichever comes first [see Dosage and Administration (2.5)].

17 PATIENT COUNSELING INFORMATION

Advise the patient to read the FDA-approved patient labeling (Patient Information and Instructions for Use).

Preparation and Administration Instructions of KYGEVVI Solution

Advise the patient to use the ZX2000 administration kit provided by the pharmacy to prepare and administer KYGEVVI solution.

Inform the patient to prepare a one-day supply of the KYGEVVI solution each morning and take each individual dose with food [see Dosage and Administration (2.4)].

Elevated Liver Transaminase Levels

Inform the patient that KYGEVVI may cause liver enzyme elevations. Instruct the patient to promptly report loss of appetite, abdominal pain, dark urine, or jaundice to his/her healthcare provider [see Warnings and Precautions (5.1)].

Gastrointestinal Adverse Reactions

Inform the patient that KYGEVVI may cause diarrhea and vomiting. Advise the patient to promptly report to his/her healthcare provider diarrhea and vomiting that lasts longer than a few days while taking KYGEVVI [see Warnings and Precautions (5.2)].

KYGEVVI manufactured for:
UCB, Inc.
Smyrna, GA 30080

KYGEVVI® is a trademark of the UCB Group of Companies.
©2025, UCB, Inc., Smyrna, GA 30080
All rights reserved.

PATIENT INFORMATION
KYGEVVI (KY-JEH-vee)
(doxecitine and doxribtimine)
powder, for oral solution

What is KYGEVVI?
KYGEVVI is a prescription medicine used for the treatment of thymidine kinase 2 deficiency (TK2d) in adults and children with a symptom onset on or before 12 years of age.

Before taking or giving KYGEVVI, tell your healthcare provider about all of your medical conditions, including if you:

- have or have had liver problems
- are pregnant or plan to become pregnant. It is not known if KYGEVVI will harm your unborn baby.
- are breastfeeding or plan to breastfeed. It is not known if KYGEVVI passes into your breast milk. Talk to your healthcare provider about the best way to feed your baby if you take KYGEVVI.

Tell your healthcare provider about all the medicines you take,including prescription and over-the-counter medicines, vitamins, and herbal supplements.

How should I take or give KYGEVVI?

- See the detailed Instructions for Usethat comes with KYGEVVI for important information about the correct way to prepare and take or give a dose of KYGEVVI.
- Take or give KYGEVVI exactly as your healthcare provider tells you. Your healthcare provider should tell you how much KYGEVVI to take or give, and when to take or give it.
- Your healthcare provider may change your or your child's dose of KYGEVVI depending on how you or your child respond to treatment and based on your or your child's weight.
- Take or give KYGEVVI 3 times a day about 6 hours apart.
- Take or give KYGEVVI with food.
- KYGEVVI may be given through a feeding tube.
- KYGEVVI comes as a packet containing powder.
  - Prepare a one-day supply of KYGEVVI solution each morning.
  - KYGEVVI should be prepared and given by adults only.
  - Do notopen the KYGEVVI packets until you are ready to use them.
  - Mix KYGEVVI powder only with room temperature water. Do notmix with any other liquids or foods.
  - Only use the dosing cup, mixing bottle, and oral syringes provided with your ZX2000 administration kit. Do notuse a household measuring cup or measuring spoon.
  If you miss a dose of KYGEVVI, take the missed dose as soon as possible. If it is within 2 hours of your next scheduled dose, do not take the missed dose. Take your next dose at your next scheduled time. Do nottake 2 doses to make up for the missed dose.
  If you spit out the dose or do not take the full dose of KYGEVVI, do nottake another dose. Take your next dose at your next scheduled time.

What are the possible side effects of KYGEVVI?
KYGEVVI may cause serious side effects, including:

- Increased liver enzyme levels.Increased liver enzyme levels in your blood are common with KYGEVVI. Your healthcare provider will do blood tests to check your liver enzyme levels before starting treatment and during treatment with KYGEVVI. Tell your healthcare provider right away if you develop any signs or symptoms of liver problems, including:

- loss of appetite
- pain on the right side of your stomach area
- dark or amber-colored urine

- yellowing of your skin or the white part of your eyes
- nausea and vomiting
- itching

- Stomach and intestinal (gastrointestinal) problems. Diarrhea and vomiting are common with KYGEVVI, but may also be severe and lead to hospitalization. Tell your healthcare provider right away if you have diarrhea or vomiting during treatment with KYGEVVI that lasts longer than a few days.

The most common side effects of KYGEVVI include:

- diarrhea
- stomach area (abdominal) pain including pain in the upper stomach area
- vomiting
- increased liver enzyme levels in your blood

Your healthcare provider may change your dose, temporarily stop, or permanently stop treatment with KYGEVVI if you develop certain side effects.
These are not all of the possible side effects of KYGEVVI. Call your doctor for medical advice about side effects. You may report side effects to FDA at 1-800-FDA-1088.

How should I store KYGEVVI?

- Store KYGEVVI packets at room temperature between 68°F to 77°F (20°C to 25°C).
- Store prepared KYGEVVI solution at room temperature between 68°F to 77°F (20°C to 25°C) orin the refrigerator between 36°F to 46°F (2°C to 8°C).
- Use KYGEVVI solution within 16 hours of preparing. Throw away (discard) any remaining solution 16 hours after preparing orafter taking or giving the 3 doses, whichever comes first.

Keep KYGEVVI and all medicines out of the reach of children.

General information about the safe and effective use of KYGEVVI.
Medicines are sometimes prescribed for purposes other than those listed in a Patient Information leaflet. Do not use KYGEVVI for a condition for which it was not prescribed. Do not give KYGEVVI to other people, even if they have the same symptoms that you have. It may harm them. You can ask your pharmacist or healthcare provider for information about KYGEVVI that is written for health professionals.

What are the ingredients in KYGEVVI?
Active ingredients:doxecitine and doxribtimine.
Inactive ingredients:colloidal silicon dioxide and magnesium stearate.

Manufactured for: UCB, Inc., Smyrna, GA 30080
KYGEVVI® is a trademark of the UCB Group of Companies.
©2025, UCB, Inc., Smyrna, GA 30080
All rights reserved.
For more information about KYGEVVI, go to www.KYGEVVI.com or call 1-844-599-2273.

This Patient Information has been approved by the U.S. Food and Drug Administration.

Issued: 11/2025

INSTRUCTIONS FOR USE

KYGEVVI (KY-JEH-vee)
(doxecitine and doxribtimine)
powder, for oral solution

Table of contents

- Instructions for use
  - Important information
- Before you start
  - Supplies for preparing and taking or giving KYGEVVI
- Important information
  - What you need to know before preparing and taking or giving KYGEVVI
  - Storing KYGEVVI packets and oral solution
- Preparing your one-day supply of KYGEVVI
  - Get supplies ready
  - Measure water and add powder from packets
  - Mix and inspect medicine
- Dosing methods
  - How to measure your individual dose
- Individual doses 50 mL or more
  - Measure and take or give your individual dose
- Individual doses less than 50 mL
  - Measure and take or give your individual dose
- Between individual doses
  - Clean up after first and second individual dose
- End-of-day clean up
  - Pour out and clean up after third individual dose
- Dosing cup maintenance
  - Replacing the seal if misplaced or damaged
- Contact information

Instructions For Use

Important information
This Instructions for Use contains information on how to prepare a one-day supply of KYGEVVI, and take or give an individual dose of KYGEVVI.

Read this Instructions for Use before taking or giving KYGEVVI and each time you get a refill. There may be new information. This information does not take the place of talking to your healthcare provider about your or your child's medical condition or treatment.

When you are prescribed KYGEVVI for the first time, you will be provided with the carton(s) of 30 KYGEVVI packets and the ZX2000 administration kit (see Figure A). Only use the dosing cup, mixing bottle, and oral syringes provided with your ZX2000 administration kit. Do notuse a household measuring cup or measuring spoon.

Figure A

Before you start

Supplies for preparing and taking or giving KYGEVVI
Carton of 30 KYGEVVI packets

Before you start

Supplies for preparing and taking or giving KYGEVVI

Important information

What you need to know before preparing and taking or giving KYGEVVI

- You will prepare a one-day supplyof KYGEVVI solution to be taken in 3 equal dosesthroughout the day (about 6 hoursapart).
- KYGEVVI solution should be prepared on the same day as taking or giving your dose.
- KYGEVVI should be prepared and given by adults only.
- Take or give KYGEVVI exactly as prescribed by your healthcare provider.
- Do notchange your dose without talking with your healthcare provider.
- Do nottake or give more than the prescribed amount of KYGEVVI solution.
- Take KYGEVVI solution with food.
- Do notuse KYGEVVI packets after the expiration date on the packet or carton.
- Only use the dosing cup, mixing bottle, and oral syringes provided with your ZX2000 administration kit. Do notuse a household measuring cup or measuring spoon.
- Each ZX2000 administration kit comes with two oral syringes. Keep the second oral syringe as a spare.
- Rinse and dry the mixing bottle and dosing cup before first use. Do notuse the dosing cup, mixing bottle, or oral syringe if it appears dirty or damaged.
- Each ZX2000 administration kit can be used for 6 months. Contact your healthcare provider when you need a replacement.
- Contact your healthcare provider or pharmacist for a replacement if your mixing bottle, dosing cup, or oral syringe is damaged or if the markings are missing or no longer readable.
- Do notuse the packets if the tamper evident seal on the carton is broken.
- Mix KYGEVVI powder only with room temperature water. Do notmix KYGEVVI powder with any other liquids or foods.
- You may have KYGEVVI solution left over after taking or giving the 3 individual doses. Throw away (discard) any remaining KYGEVVI solution 16 hours after preparing or after taking or giving the 3 doses, whichever comes first.
- If powder spills out of a packet before use, do notuse the packet. Throw it awayand use a new KYGEVVI packet.
- If KYGEVVI solution comes in contact with your eyes or skin, rinse under cold water and contact your healthcare provider.

- KYGEVVI solution is compatible with most feeding tubes. Follow the steps in this Instructions for Use booklet to prepare your one-day supply of KYGEVVI. Then follow the feeding tube manufacturer instructions on how to give KYGEVVI using a feeding tube.
  - Draw up the prescribed individual dose using a syringe compatible with the feeding tube. Give the KYGEVVI solution right away through the feeding tube.
  - Flush any remaining KYGEVVI solution in the syringe or feeding tube until no solution is left. Ask your healthcare provider how much water to use.
  - Throw away (discard) any remaining KYGEVVI solution 16 hours after preparing or after taking or giving the 3 doses, whichever comes first.

Important information

Storing KYGEVVI packets and oral solution:

- Store KYGEVVI packets at room temperature between 68°F to 77°F (20°C to 25°C).
- Store the prepared KYGEVVI solution at room temperature between 68°F to 77°F (20°C to 25°C) orin the refrigerator between 36°F to 46°F (2°C to 8°C).
- Make sure the dosing cup is screwed on tightly to the mixing bottle when storing your KYGEVVI solution to avoid spills or leaks.
- When storing or carrying the KYGEVVI solution, keep the mixing bottle upright.
- Use the KYGEVVI solution within 16 hours of preparing. Throw away (discard) any remaining solution 16 hours after preparing or after taking or giving the 3 doses, whichever comes first.
- Keep KYGEVVI and all medicines out of the reach of children.

Preparing your one-day supply of KYGEVVI

Get supplies ready

Step 1

- Wash your hands well with soap and water.
- Place the mixing bottle, dosing cup, and oral syringe (if you need one to measure your individual dose) on a clean, well-lit flat work surface. If the dosing cup is attached to the mixing bottle, unscrew it from the mixing bottle and set it down (see Figure B).
- Make sure "KYGEVVI" appears on the carton.
- Check the expiration date printed on the bottom of the KYGEVVI carton. When opening the KYGEVVI carton for the first time, break the tamper evident seal.
- Remove the prescribed number of KYGEVVI packets needed for your one-day supply of KYGEVVI out of the carton. Your one-day supply of KYGEVVI will be divided into 3 individual doses.
- Do notopen the KYGEVVI packets until Step 2.

Figure B

Preparing your one-day supply of KYGEVVI

Measure water and add powder from packets

Step 2

- On a flat surface, pour the prescribed amount of room temperature water into the mixing bottle (see Figure C).
  - Do notpour the water into the dosing cup.
  - Important: Do notadd the powder from the packets to the mixing bottle before this step.
- Check to make sure the mixing bottle is filled with water up to the marking that matches the amount prescribed by your healthcare provider. The marking should also match the number of packets needed for your one-day supply (see Figure C).
- Check you have counted out the correct number of KYGEVVI packets for your one-day supply, as shown on your prescription.
- Tap the packet on a hard surface to settle the powder to the bottom of the packet away from the dotted line (see Figure D).
- Carefully fold and tear or cut along the dotted line (see Figure E). If you spill any powder, do notuse it. Throw the packet away and use a new packet.
- Empty the entire packet contents into the mixing bottle containing water. Be careful not to drop the packet into the mixing bottle (see Figure F).
- Pour only 1 packet into the mixing bottle at a time. Repeat Steps 2dto 2f, for each packet until you have poured the prescribed number of packets for your one-day supply.

Figure C

Figure D

Figure E

Figure F

Preparing your one-day supply of KYGEVVI

Mix and inspect medicine

Step 3

- Screw the dosing cup tightly onto the mixing bottle (see Figure G).
- Place one hand at the end of the mixing bottle and the other hand at the end of the dosing cup. Gently turn the mixing bottle upside down and back at least 20 times(see Figure H).
- Check the solution. If you see any powder, keep turning the mixing bottle upside down and back until the powder dissolves (see Figure I).
  - The mixed solution may be cloudy and have some remaining powder at the bottom or top. This is normal.

You have now prepared your one-day supply of KYGEVVI solution for 3 individual doses. Take KYGEVVI solution with food.

Figure G

Figure H

Figure I

Dosing methods

How to measure your individual dose

There are 2 different methods to take or give KYGEVVI solution depending on your individual dose. Use the table below to identify which steps you should follow:

Individual doses 50 mL or more | Individual doses lessthan 50 mL (dosing cup used for dose preparation only)
Example 100 mL | Example 14 mL
Use dosing cup Follow Step 4 | Use oral syringe Follow Step 5

Individual doses 50 mL or more

Measure and take or give your individual dose

Step 4: Dosing cup

- Check to make sure the dosing cup is screwed on tightly to the mixing bottle.
- Mix the already prepared solution by slowly turning the mixing bottle upside down and back at least 3 times.
- Unscrew the dosing cup from the mixing bottle and place it on a flat surface.
- Pour KYGEVVI solution from the mixing bottle into the dosing cup until it reaches the marking on the dosing cup for your prescribed individual dose (see Figure J). Note:Your dose may be different than the dose shown in Figure J.
- Drink or give the entire solution from the dosing cup (see Figure K).
- When it is time for the second or third individual dose, repeat Steps 4ato 4efor each individual dose.
- After the first or second individual dose, go to Step 6for instructions on how to clean your supplies and store KYGEVVI solution. After the third individual dose, go to Step 7for instructions on how to clean your supplies and dispose of unused KYGEVVI solution.

Figure J

Figure K

Individual doses less than 50 mL

Measure and take or give your individual dose

Step 5: Oral syringe

If your individual dose is more than 10 mL, you will need to use the same oral syringe more than 1 time.

- Check to make sure the dosing cup is screwed on tightly to the mixing bottle.
- Mix the already prepared solution by slowly turning the mixing bottle upside down and back at least 3 times.
- Unscrew the dosing cup from the mixing bottle and place on a flat surface.
- Pour slightly more than the amount of KYGEVVI solution needed for your prescribed individual dose into the dosing cup (see Figure L).
- Push the plunger of the oral syringe all the way down to make sure there is no air in the oral syringe when measuring the dose (see Figure M).
- Place the tip of the oral syringe into the dosing cup with the oral solution. Fill the oral syringe by pulling the plunger back until it reaches the marking on the oral syringe that matches your prescribed individual dose (see Figure N).
  Note:If your individual dose is more than 10 mL, you will need to use the same oral syringe more than 1 time. Follow your healthcare provider's instructions on how to measure your dose.
  Figure L
  Figure M
  Figure N
- Place the tip of the oral syringe into the mouth and point the tip towards the inside of either cheek (see Figure O).
  - If you are giving KYGEVVI to a young child, the child must be seated and held in place to prevent the oral solution from going down the wrong way or choking.
- Slowly push the plunger all the way down until the oral syringe is empty (see Figure O).
  Figure O
- If your prescribed individual dose is more than 10 mL, repeat Steps 5dto 5huntil you take or give the full individual dose.
- Pour back any remaining solution from the dosing cup into the mixing bottle.
- When it is time for the second or third individual dose, repeat Steps 5ato 5jfor each individual dose.
- After the first or second individual dose, go to Step 6for instructions on how to clean your supplies and store KYGEVVI solution. After the third individual dose, go to Step 7for instructions on how to clean your supplies and dispose of unused KYGEVVI solution.

Between individual doses
Clean up after first and second individual dose

Step 6
After you complete the first or second individual dose:

- Rinse the dosing cup with cold water after each use (see Figure P).
- Dry the dosing cup with a clean, dry towel.
- After the dosing cup is dry, screw the dosing cup tightly onto the mixing bottle (see Figure Q) and store it at room temperature or in the refrigerator until it is time for the next individual dose.
- If you used the oral syringe, clean it with cold water:
  - Rinse the oral syringe with cold water by filling the oral syringe with water and pushing it back out (see Figure R). Then remove the plunger from the barrel and rinse the plunger and barrel under running tap water until it is clean (see Figure R).
  - Let the oral syringe barrel and plunger dry in the open air. After the oral syringe barrel and plunger are dry, put the plunger back into the barrel.
- Do notwash the dosing cup or oral syringe in the dishwasher.

Figure P

Figure Q

Figure R

End-of-day clean up

Pour out and clean up after third individual dose

Step 7
After you take or give the third individual dose, throw away any remaining KYGEVVI solution in the sink.
Do not save KYGEVVI solution for another day.

- Remove the seal from the dosing cup to thoroughly clean it (see Figure S).
- Clean the mixing bottle, dosing cup and seal by hand with soap and warm water. Use a brush to remove any residue left in the mixing bottle or dosing cup (see Figure T).
- Dry the mixing bottle, dosing cup and seal with a clean towel. Put the dry seal back into the dosing cup, with the thin side of the sealfacing the groove.
- If you used the oral syringe, clean it with cold water:
  - Rinse the oral syringe with cold water by filling the oral syringe with water and pushing it back out (see Figure U). Then remove the plunger from the barrel and rinse the plunger and barrel under running tap water until it is clean (see Figure U).
  - Let the oral syringe barrel and plunger dry in the open air. After the oral syringe barrel and plunger are dry, put the plunger back into the barrel.
- Do notwash the mixing bottle, dosing cup, seal, or oral syringe in the dishwasher.
- Store all supplies in a clean, dry area out of the reach of children for the next day's use.

Figure S

Figure T

Figure U

Dosing cup maintenance

Replacing the seal if misplaced or damaged

Changing the dosing cup seal

If you misplace the dosing cup seal or you notice leakage when the dosing cup is screwed on tightly to the mixing bottle, change the seal using one of the two spare seals provided in the ZX2000 administration kit. Follow these steps to replace the seal:

- Remove the seal in the dosing cup (see Figure V). Skip this step if you misplaced the seal.
- Wash the dosing cup groove with warm water (see Figure W).
- Get a new seal from the spare seal box (see Figure X).
- Insert the seal into the groove of the dosing cup with the thin side of the sealfacing the groove (see Figure Y).

Figure V

Figure W

Figure X

Figure Y

Contact Information

Contact your healthcare provider or pharmacist if you have any questions about this Instructions for Use. You may also contact UCBCares at 1-844-599-CARE (2273) for assistance.

KYGEVVI manufactured for: UCB, Inc., Smyrna, GA 30080
This Instructions for Use has been approved by the U.S. Food and Drug Administration.
Approved: 11/2025

PRINCIPAL DISPLAY PANEL - 30 Packet Carton

NDC 50474-350-30
Rx only

kygevvi®

(doxecitine and doxribtimine)
Powder for Oral Solution

2 g/2 g per packet

Only use the dosing cup, mixing bottle, and oral syringes
provided with your separate ZX2000 administration kit.

See enclosed Instructions for Use for important preparation
and administration instructions.

30 packets

Each 4 g packet contains 2 g doxecitine and 2 g doxribtimine.